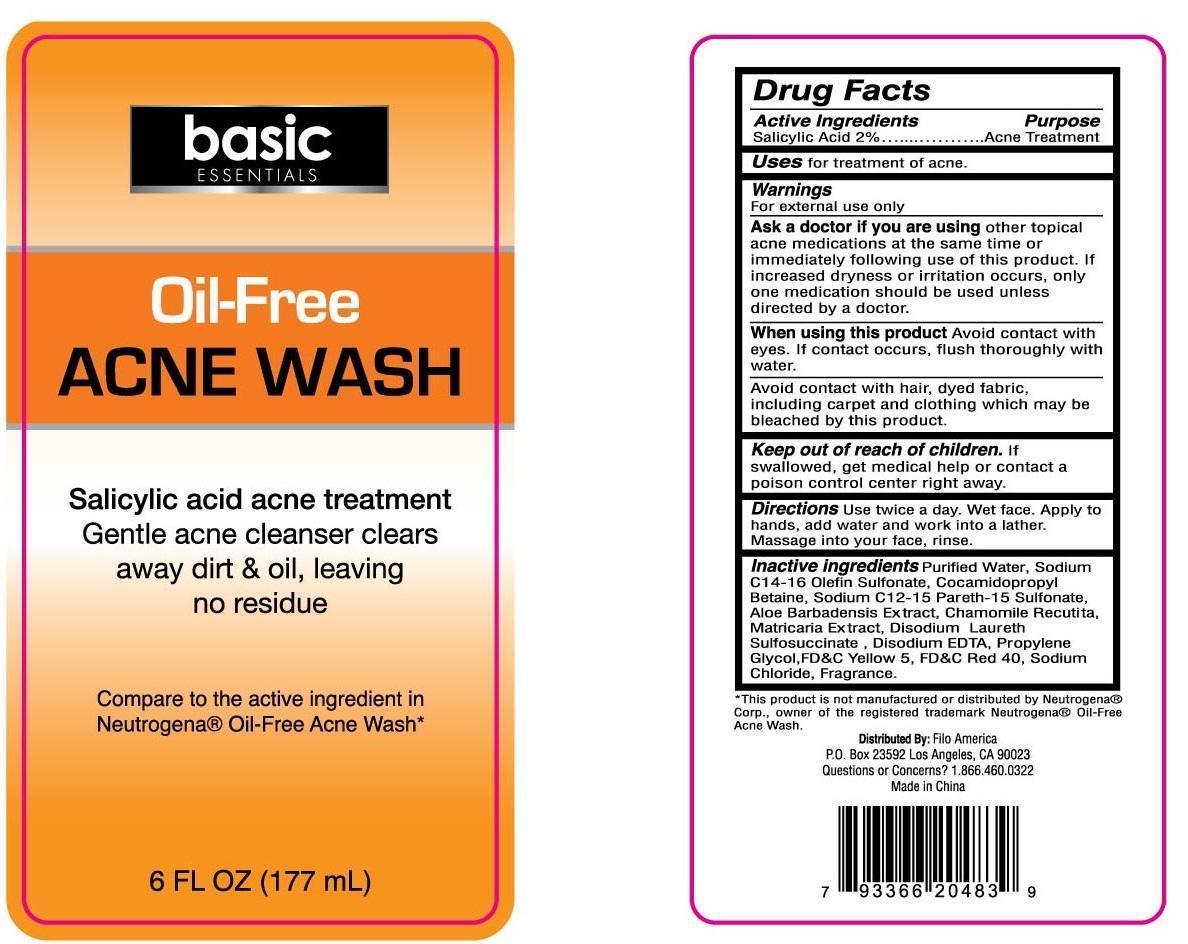 DRUG LABEL: Oil-Free Acne Wash
NDC: 50438-210 | Form: LOTION
Manufacturer: Filo America
Category: otc | Type: HUMAN OTC DRUG LABEL
Date: 20131205

ACTIVE INGREDIENTS: Salicylic acid 20 mg/1 mL
INACTIVE INGREDIENTS: water; SODIUM C14-16 OLEFIN SULFONATE; COCAMIDOPROPYL BETAINE; SODIUM C12-15 PARETH-15 SULFONATE; ALOE VERA LEAF; CHAMAEMELUM NOBILE FLOWER; CHAMOMILE; LINOLEAMIDOPROPYL PG-DIMONIUM CHLORIDE PHOSPHATE; EDETATE DISODIUM; PROPYLENE GLYCOL; FD&C YELLOW NO. 5; FD&C RED NO. 40; SODIUM CHLORIDE

Active ingredients

Salicylic acid 2%

Purpose

Acne medication

Use

For the treatment of acne

warnings

For external use only

When using this product

- Ask a doctor if you are using other topical acne medications at the same time or immediately following use of this product. if increased dryness or irritation occurs, only one medication should be used unless directed by doctor.
- Avoid contact with eyes. If contact occurs, flush thoroughlywith water.
- Avoid contact with hair, dyed fabric, including carpet and clothing which may be bleached by this product.

Keep out of reach of children

If swallowed, get medical help or contact a Poison Control Center right away.

Directions

- use twice a day
- wet face. Apply to hands, add water and work into lather. massage into your face, rinse.

Inactive ingredients

water, sodium C14-16 olefin sulfonate, cocamidopropyl betaine, sodium C12-15 pareth-15 sulfonate, aloe barbadensis leaf extract, anthemis nobilis flower extract, matricaria (chamomilla recutita) flower extract, linoleamidopropyl PG-dimonium chloride phosphate, disodium EDTA, propylene glycol, yellow 5, red 40, sodium chloride, fragrance

Disclaimer

This product is not manufactured or distributed by Neutrogena Corporation

Principal Display Panel

Salicylic acid acne treatment

Gentle acne cleanser clears

away dirt & Oil, leaving no residue

Compare to the active ingredient in Neutrogena Oil-Free Acne Wash